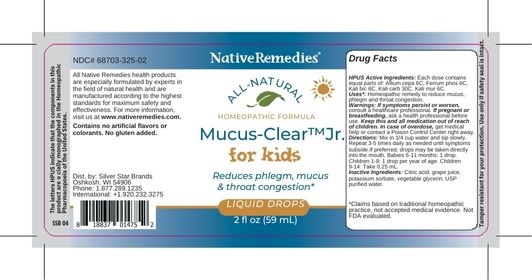 DRUG LABEL: Mucus-Clear Jr.
NDC: 68703-325 | Form: LIQUID
Manufacturer: Silver Star Brands
Category: homeopathic | Type: HUMAN OTC DRUG LABEL
Date: 20250101

ACTIVE INGREDIENTS: POTASSIUM CARBONATE 30 [hp_C]/59 mL; POTASSIUM CHLORIDE 6 [hp_C]/59 mL; FERROSOFERRIC PHOSPHATE 6 [hp_C]/59 mL; ONION 6 [hp_C]/59 mL; POTASSIUM DICHROMATE 6 [hp_C]/59 mL
INACTIVE INGREDIENTS: POTASSIUM SORBATE; WATER; CONCORD GRAPE JUICE; GLYCERIN; ANHYDROUS CITRIC ACID

NativeRemedies® Mucus-Clear™ Jr.

HPUS Active Ingredients: Each dose contains equal parts of: Allium cepa 6C, Ferrum phos 6C, Kali bic 6C, Kali carb 30C, Kali mur 6C.

The letters HPUS indicate that the components in this product are officially monographed in the Homeopathic Pharmacopoeia of the United States.

Uses*

Uses*: Homeopathic remedy to reduce mucus, phlegm, throat congestion.

*Claims based on traditional homeopathic practice, not accepted medical evidence. Not FDA evaluated.

Warnings

Warnings: If symptoms persist or worsen, consult a healthcare professional. If pregnant or breastfeeding, ask a health professional before use. Keep this and all medication out of reach of children. In case of overdose, get medical help or contact a Poison Control Center right away.

Directions

Directions: Mix in 1/4 cup water and sip slowly. Alternatively, drops may be taken directly into the mouth. Babies 6-11 months: 1 drop. Children 1-8: 1 drop per year of age. Children 9-14: Take 0.25 mL. Repeat 3-5 times daily as needed until symptoms subside.

OTHER SAFETY INFORMATION

Contains no artificial flavors or colorants. No gluten added.

Tamper resistant for your protection. Use only if safety seal is intact.

Inactive Ingredients

Inactive Ingredients: Citric acid, grape juice, potassium sorbate, vegetable glycerin, USP purified water.

KEEP OUT OF REACH OF CHILDREN

Keep this and all medication out of reach of children.

PREGNANCY OR BREAST FEEDING

If pregnant or breastfeeding, ask a health professional before use.

PURPOSE

Temporarily relieves common cold symptoms in children.